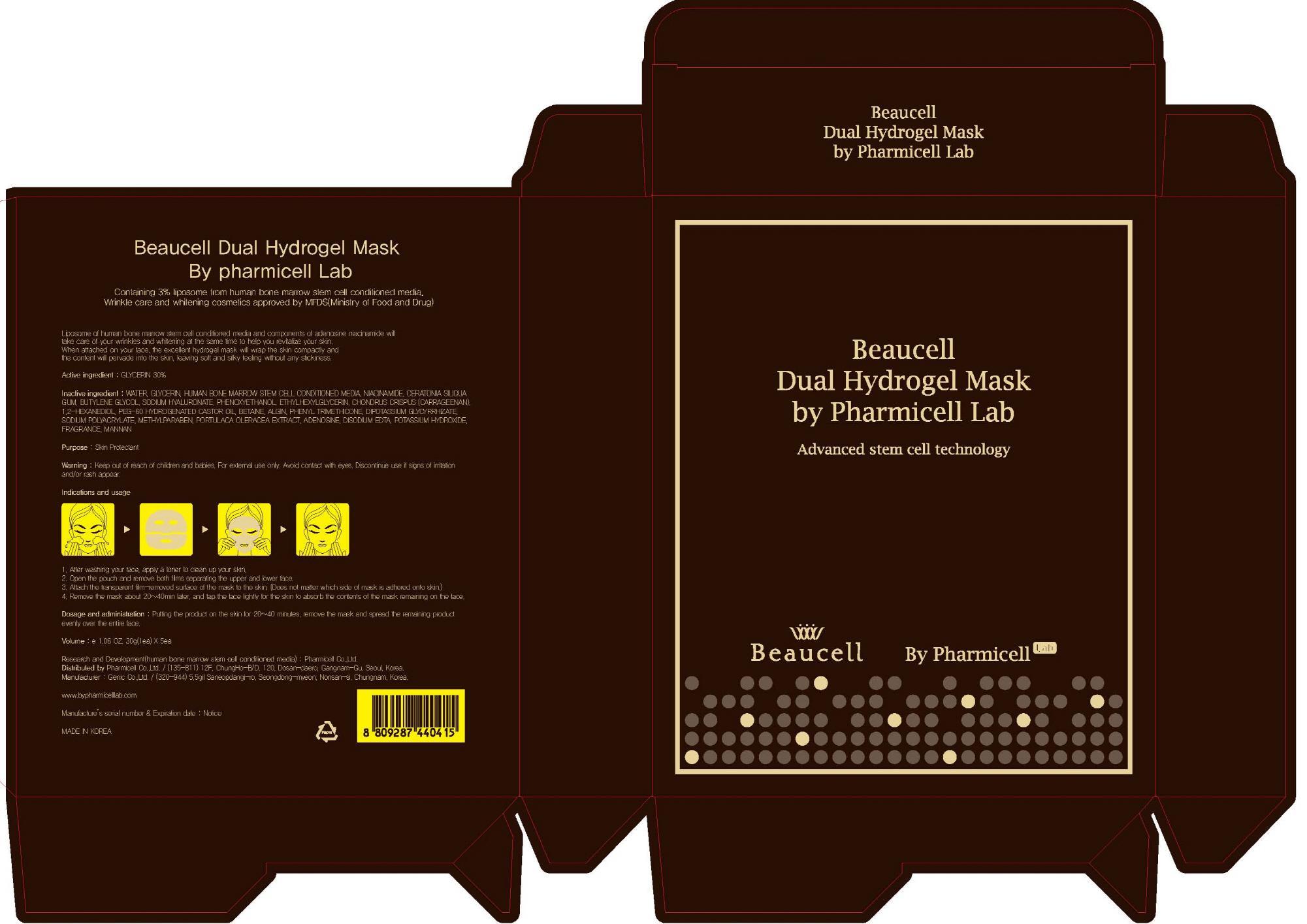 DRUG LABEL: By Pharmicell Lab Beaucell Dual Hydrogel Mask
NDC: 60949-110 | Form: PATCH
Manufacturer: Pharmicell Co., Ltd.
Category: otc | Type: HUMAN OTC DRUG LABEL
Date: 20130709

ACTIVE INGREDIENTS: GLYCERIN 9 g/5 1
INACTIVE INGREDIENTS: WATER; BUTYLENE GLYCOL

ACTIVE INGREDIENT

Active ingredient : GLYCERIN 30%

INACTIVE INGREDIENT

Inactive ingredient : WATER, HUMAN BONE MARROW STEM CELL CONDITIONED MEDIA, NIACINAMIDE, CERATONIA SILIQUA GUM, BUTYLENE GLYCOL, SODIUM HYALURONATE, PHENOXYETHANOL, ETHYLHEXYLGLYCERIN, CHONDRUS CRISPUS (CARRAGEENAN), 1,2-HEXANEDIOL, PEG-60 HYDROGENATED CASTOR OIL, BETAINE, ALGIN, PHENYL TRIMETHICONE, DIPOTASSIUM GLYCYRRHIZATE, SODIUM POLYACRYLATE, METHYLPARABEN, PORTULACA OLERACEA EXTRACT, ADENOSINE, DISODIUM EDTA, POTASSIUM HYDROXIDE, FRAGRANCE, MANNAN

PURPOSE

Purpose : Skin Protectant

WARNINGS

Warning : Keep out of reach of children and babies. For external use only. Avoid contact with eyes. Discontinue use if signs of irritation and/or rash appear.

Keep out of reach of children and babies.

INDICATIONS AND USAGE

1. After washing your face, apply a toner to clean up your skin.

2. Open the pouch and remove both films separating the upper and lower face.

3. Attach the transparent film-removed surface of the mask to the skin. (Does not matter which side of mask is adhered onto skin.)

4. Remove the mask about 20-40min later, and tap the face lightly for the skin to absorb the contents of the mask remaining on the face.

Dosage and administration : Putting the product on the skin for 20-40 minutes, remove the mask and spread the remaining product evenly over the entire face.